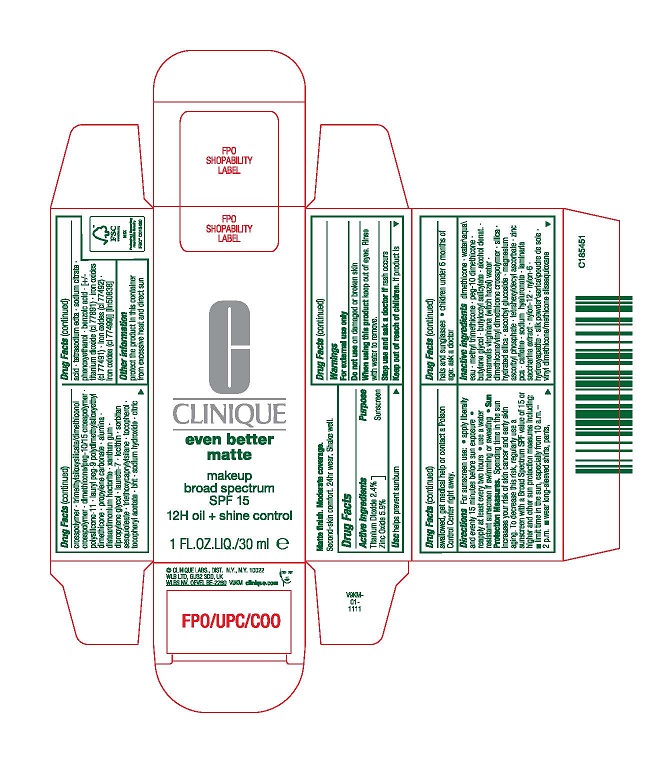 DRUG LABEL: CL EB MATTE MAKEUP BROAD SPECTRUM SPF 15
NDC: 49527-113 | Form: EMULSION
Manufacturer: CLINIQUE LABORATORIES LLC
Category: otc | Type: HUMAN OTC DRUG LABEL
Date: 20231020

ACTIVE INGREDIENTS: ZINC OXIDE 59 mg/1 mL; TITANIUM DIOXIDE 24 mg/1 mL
INACTIVE INGREDIENTS: ASCORBYL GLUCOSIDE; POLICAPRAM; SILICON DIOXIDE; HYALURONATE SODIUM; SACCHARINA LATISSIMA; BENZOIC ACID; VINYL DIMETHICONE/METHICONE SILSESQUIOXANE CROSSPOLYMER; DIMETHICONE/PEG-10/15 CROSSPOLYMER; PROPYLENE CARBONATE; EDETATE SODIUM; METHYL TRIMETHICONE; BUTYLOCTYL SALICYLATE; NYLON-12; BOMBYX MORI FIBER; XANTHAN GUM; SODIUM CITRATE; DIMETHICONE; WATER; ALUMINUM OXIDE; LECITHIN, SOYBEAN; ALCOHOL; PEG-10 DIMETHICONE (220 CST); BUTYLENE GLYCOL; HAMAMELIS VIRGINIANA TOP WATER; DIMETHICONE/VINYL DIMETHICONE CROSSPOLYMER (HARD PARTICLE); HYDRATED SILICA; TETRAHEXYLDECYL ASCORBATE; ZINC PIDOLATE; CAFFEINE; TRIBASIC CALCIUM PHOSPHATE; DIMETHICONE/VINYL DIMETHICONE CROSSPOLYMER (SOFT PARTICLE); LAURYL PEG-9 POLYDIMETHYLSILOXYETHYL DIMETHICONE; DISTEARDIMONIUM HECTORITE; DIPROPYLENE GLYCOL; LAURETH-7; SORBITAN SESQUIOLEATE; BUTYLATED HYDROXYTOLUENE; TRIETHOXYCAPRYLYLSILANE; TOCOPHEROL; ALPHA-TOCOPHEROL ACETATE; SODIUM HYDROXIDE; PHENOXYETHANOL; FERRIC OXIDE RED; FERRIC OXIDE YELLOW; FERROSOFERRIC OXIDE

CL EB MATTE MAKEUP BROAD SPECTRUM SPF 15

Active Ingredient

Titanium Dioxide 2.4%

Zinc Oxide 5.9%

Purpose

Sunscreen

Use

helps prevent sunburn

Warnings

For External use only

Do not use

on damaged or broken skin

When using this product

keep out of eyes. Rinse with water to remove.

Stop use and ask a doctor if

rash occurs

Keep out of reach of children

If product is swallowed, get medical help or contact a Poison Control Center right away

Directions

For sunscreen use:
apply liberally 15 minutes before sun exposure
reapply at least every two hours
use a water resistant sunscreen if swimming or sweating
Sun Protection Measures. Spending time in the sun increases your risk of skin cancer and early skin aging. To decrease this risk, regularly use a sunscreen with a Broad Spectrum SPF value of 15 or higher and other sun protection measures including:
limit time in the sun, especially from 10 a.m.–2 p.m.
wear long-sleeved shirts, pants, hats and sunglasses
children under 6 months of age: ask a doctor

Inactive Ingredients

dimethicone,water\aqua\eau,methyl trimethicone,peg-10 dimethicone,butylene glycol,butyloctyl salicylate,alcohol denat.,hamamelis virginiana (witch hazel) water,dimethicone/vinyl dimethicone crosspolymer,silica,hydrated silica,ascorbyl glucoside,magnesium ascorbyl phosphate,tetrahexyldecyl ascorbate,zinc pca,caffeine,sodium hyaluronate,laminaria saccharina extract,nylon-12,nylon-6,hydroxyapatite,silk powder\serica\poudre de soie,vinyl dimethicone/methicone silsesquioxane crosspolymer,trimethylsiloxysilicate/dimethiconol crosspolymer,dimethicone/peg-10/15 crosspolymer,polysilicone-11,lauryl peg-9 polydimethylsiloxyethyl dimethicone,propylene carbonate,alumina,disteardimonium hectorite,xanthan gum,dipropylene glycol,laureth-7,lecithin,sorbitan sesquioleate,triethoxycaprylylsilane,tocopherol,tocopheryl acetate,bht,sodium hydroxide,citric acid,tetrasodium edta,sodium citrate,phenoxyethanol,benzoic acid, [+/- titanium dioxide (ci 77891),iron oxides (ci 77491),iron oxides (ci 77492),iron oxides (ci 77499)] <iln50838>

Other Information

protect the product in this container from excessive heat and direct sun

Principal Display Panel

CLINIQUE

even better matte

makeup broad spectrum SPF15

12H oil + shine control

1 FL.OZ.LIQ/30ml